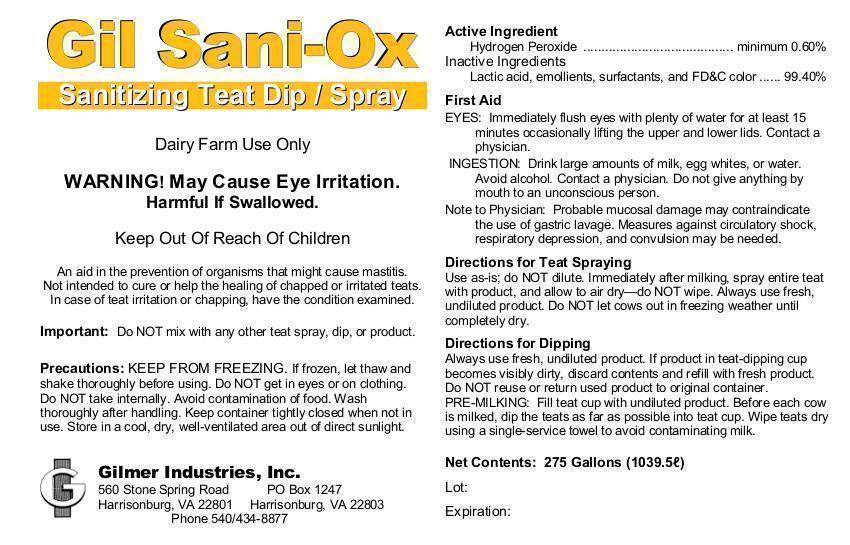 DRUG LABEL: Gil Sani-Ox
NDC: 54420-011 | Form: LIQUID
Manufacturer: Gilmer Industries, Inc.
Category: animal | Type: OTC ANIMAL DRUG LABEL
Date: 20150601

ACTIVE INGREDIENTS: HYDROGEN PEROXIDE 6000.0000 mg/1 L

Gil Sani-Ox

PURPOSE

Sanitizing Teat Dip / Spray

Dairy Farm Use Only

WARNING! May Cause Eye Irritation. Harmful If Swallowed.

Keep Out Of Reach Of Children

An aid in the prevention of organisms that might cause mastitis.

Not intended to cure or help the healing of chapped or irritated teats.

In case of teat irritation or chapping, have the condition examined.

Important: Do NOT mix with any other teat spray, dip, or product.

Precautions: KEEP FROM FREEZING. If frozen, let thaw and shake thoroughly before using. Do NOT get in eyes or on clothing. Do NOT take internally. Avoid contamination of food. Wash thoroughly after handling. Keep container tightly closed when not in use. Store in a cool, dry, well-ventilated area out of direct sunlight.

Active Ingredient

Hydrogen Peroxide ......................................................... 0.60%

Inactive Ingredients

Lactic acid, emollients, surfactants, and FD&C color.... 99.40%

USER SAFETY WARNINGS

First Aid

EYES: Immediately flush eyes wtih plenty of water for at least 15 minutes occassionally lifting the upper and lower lids. Contact a physician.

INGESTION: Drink large amounts of milk, egg whites, or water. Avoid alcohol. Contact a physician. Do not give anything by mouth to an unconscious person.

Note to Physician: Probable mucosal damage may contraindicate the use of gastric lavage. Measures against circulatory shock, respiratory depression, and convulsion may be needed.

DOSAGE AND ADMINISTRATION

Directions for Teat Spraying

Use as-is; do NOT dilute.
Immediately after milking, spray entire teat with product, and allow to air dry—do NOT wipe.
Always use fresh, undiluted product.
Do NOT let cows out in freezing weather until completely dry.

Directions for Dipping

Always use fresh, undiluted product.
If product in teat-dipping cup becomes visibly dirty, discard contents and refill with fresh product.
Do NOT reuse or return used product to original container.
PRE-MILKING: Fill teat cup with undiluted product.
Before each cow is milked, dip the teats as far as possible into teat cup.
Wipe teats dry using a single-service towel to avoid contaminating milk.